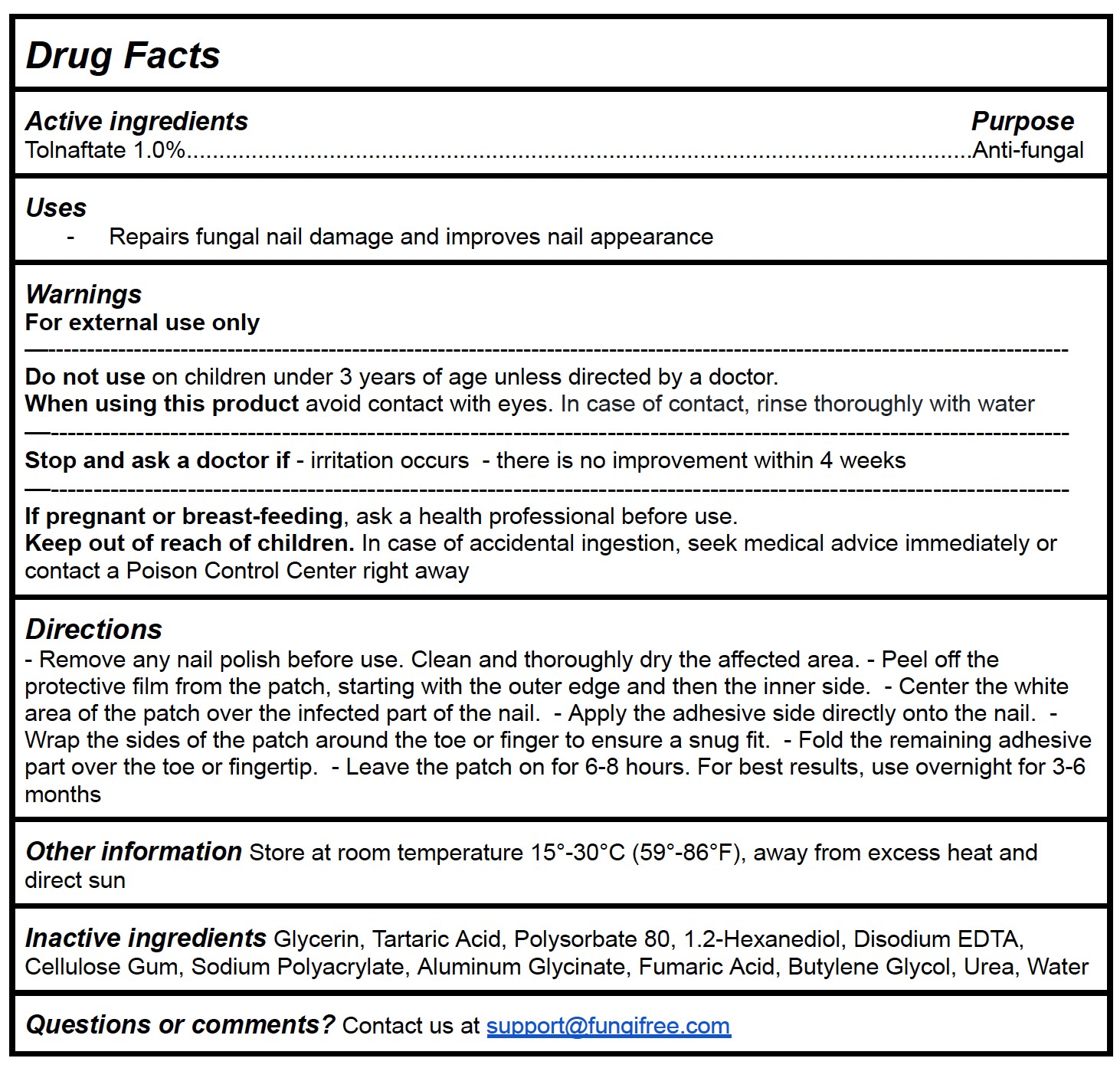 DRUG LABEL: FungiFree Fungal Nail Patches
NDC: 83364-013 | Form: PATCH
Manufacturer: YITONGBADA (SHENZHEN) INTERNATIONAL TRADE CO., LTD
Category: otc | Type: HUMAN OTC DRUG LABEL
Date: 20260128

ACTIVE INGREDIENTS: TOLNAFTATE 1 g/100 g
INACTIVE INGREDIENTS: 1,2-HEXANEDIOL; ALUMINUM GLYCINATE; CELLULOSE GUM; TARTARIC ACID; EDETATE DISODIUM; UREA; GLYCERIN; BUTYLENE GLYCOL; WATER; POLYSORBATE 80; SODIUM POLYACRYLATE (2500000 MW); FUMARIC ACID

Directions

- Remove any nail polish before use. Clean and thoroughly dry the affected area. - Peel off the protective film from the patch, starting with the outer edge and then the inner side. - Center the white area of the patch over the infected part of the nail. - Apply the adhesive side directly onto the nail. - Wrap the sides of the patch around the toe or finger to ensure a snug fit. - Fold the remaining adhesive part over the toe or fingertip. - Leave the patch on for 6-8 hours. For best results, use overnight for 3-6 months

Other information Store at room temperature 15°-30°C (59°-86°F), away from excess heat and direct sun

INACTIVE INGREDIENT

Inactive ingredients Glycerin, Tartaric Acid, Polysorbate 80, 1.2-Hexanediol, Disodium EDTA, Cellulose Gum, Sodium Polyacrylate, Aluminum Glycinate, Fumaric Acid, Butylene Glycol, Urea, Water

Drug Facts

Active ingredients

Tolnaftate 1.0%

PURPOSE

Anti-fungal

INDICATIONS AND USAGE

Repairs fungal nail damage and improves nail appearance

Do not use on children under 3 years of age unless directed by a doctor.

When using this product avoid contact with eyes. In case of contact, rinse thoroughly with water

ASK DOCTOR

Stop and ask a doctor if - irritation occurs - there is no improvement within 4 weeks

PREGNANCY OR BREAST FEEDING

If pregnant or breast-feeding, ask a health professional before use.

Keep out of reach of children. In case of accidental ingestion, seek medical advice immediately or contact a Poison Control Center right away

Warnings

For external use only